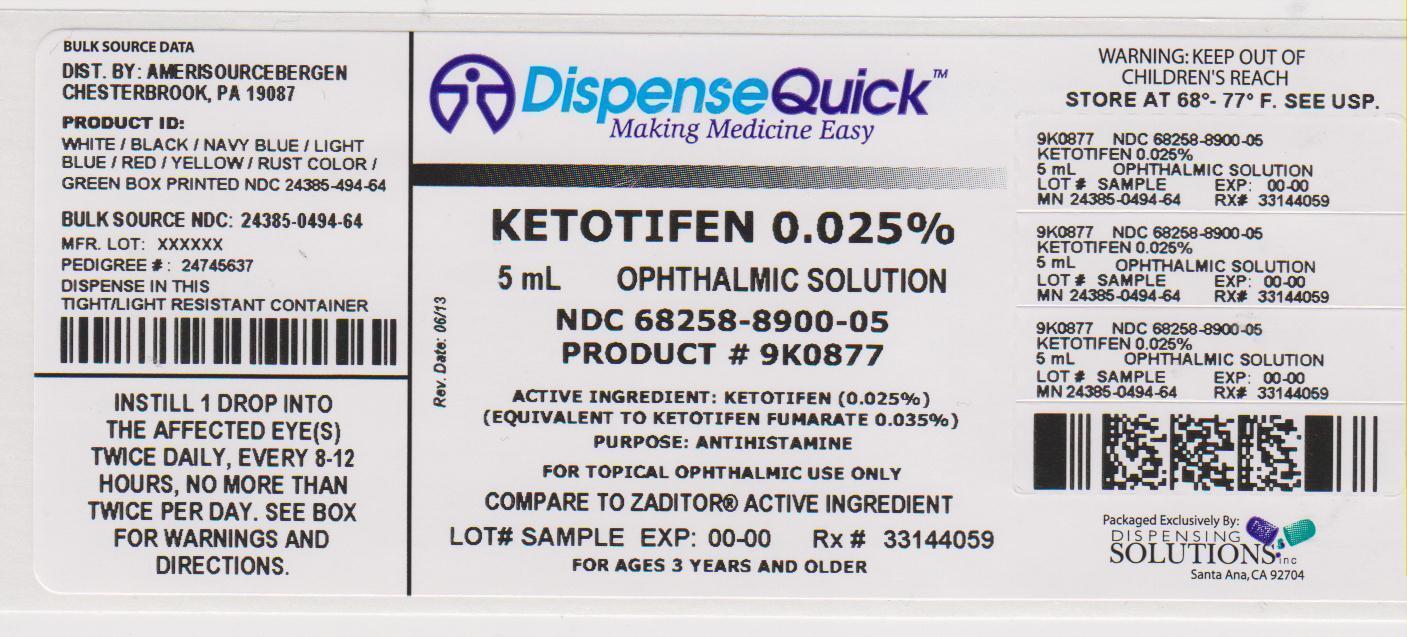 DRUG LABEL: good neighbor pharmacy eye itch relief
NDC: 68258-8900 | Form: SOLUTION
Manufacturer: Dispensing Solutions, Inc.
Category: otc | Type: HUMAN OTC DRUG LABEL
Date: 20130718

ACTIVE INGREDIENTS: KETOTIFEN FUMARATE 0.25 mg/1 mL
INACTIVE INGREDIENTS: GLYCERIN; WATER; HYDROCHLORIC ACID; SODIUM HYDROXIDE

Amerisource Bergen Eye Itch Relief Drug Facts

Active ingredient

Ketotifen (0.025%)

(equivalent to ketotifen fumarate 0.035%)

Purpose

Antihistamine

Use

Temporarily relieves itchy eyes due to pollen, ragweed, grass, animal hair and dander.

Warnings

Do not use

. If solution changes color or becomes cloudyi

. If you are sensitive to any ingredient in this product

. To treat contact lens related irritation

When using this product

. Do not touch tip of container to any surface to avoid contamination

. Remove contact lenses before use

. Wait at least 10 minutes before reinserting contact lenses after use

. Replace cap after each use

Stop use and ask a doctor if

you experience any of the following:

. Eye pain

. Changes in vision

. Redness of the eye

. Itching worsens or lasts for more than 72 hours

Keep out of reach of children.

If swallowed, get medical help or contact a Poison Control Center right away. (1-800-222-1222)

Directions

. Adults and children 3 years of age and older: Put 1 drop in the affected eye(s) twice daily, every 8-12 hours, no more than twice per day.

. Children under 3 years of age: Consult a doctor.

Other information

. Only for use in the eye

. Store at 20-25°C (68-77°F) [see USP Controlled Room Temperature]

Inactive ingredients

benzalkonium chloride 0.01%, glycerin, purified water. May contain hydrochloric acid and/or sodium hydroxide (to adjust pH).

Questions or comments?

1-800-719-9260

PACKAGE LABEL PRINCIPAL DISPLAY PANEL

NDC 68258-8900-05